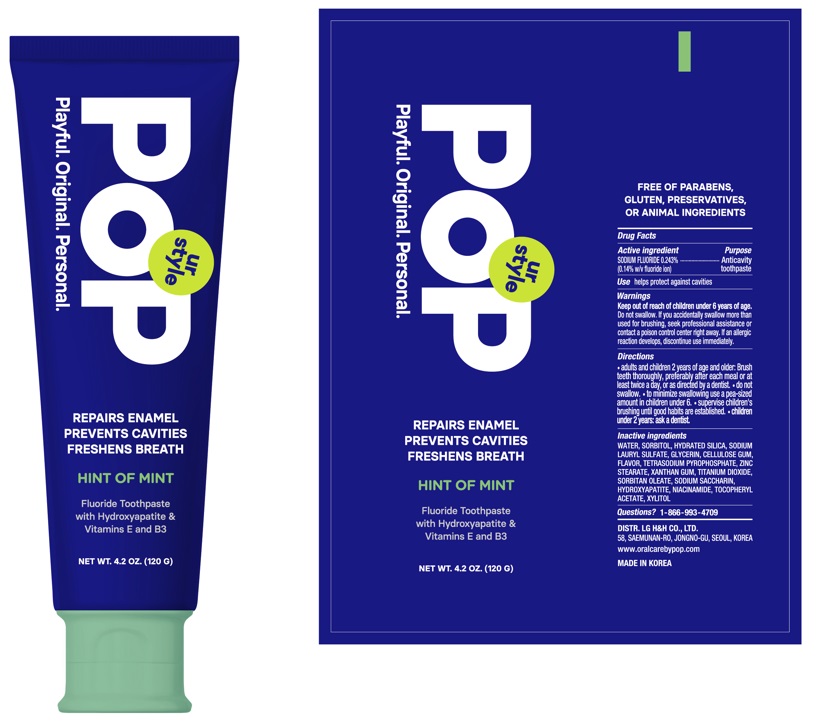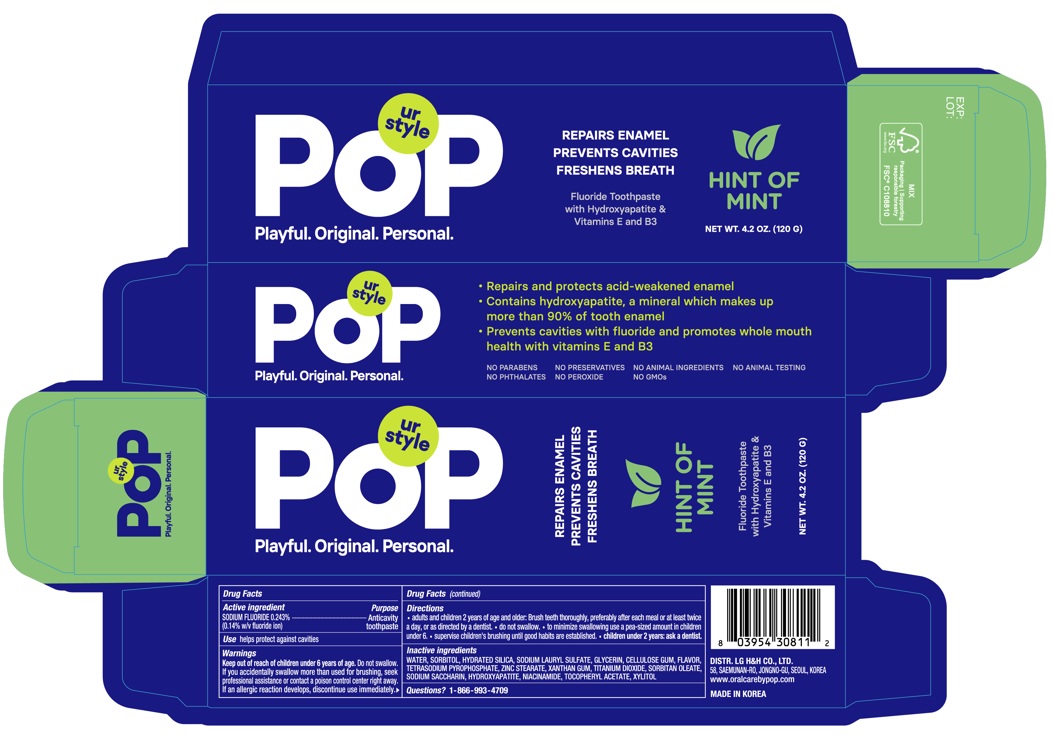 DRUG LABEL: POP Hint Of Mint
NDC: 53208-571 | Form: PASTE, DENTIFRICE
Manufacturer: LG H&H Co., Ltd.
Category: otc | Type: HUMAN OTC DRUG LABEL
Date: 20250101

ACTIVE INGREDIENTS: SODIUM FLUORIDE 1.4 mg/1 g
INACTIVE INGREDIENTS: SORBITOL; SORBITAN MONOOLEATE; TRIBASIC CALCIUM PHOSPHATE; NIACINAMIDE; .ALPHA.-TOCOPHEROL ACETATE, DL-; WATER; ZINC STEARATE; GLYCERIN; SODIUM PYROPHOSPHATE; POLOXAMER 407; SODIUM LAURYL SULFATE; XANTHAN GUM; SACCHARIN SODIUM; SUCRALOSE; TITANIUM DIOXIDE; XYLITOL; HYDRATED SILICA

53208-571-20 POP Hint Of Mint Toothpaste 120g

Drug Facts

Active Ingredient

SODIUM FLUORIDE 0.243% (0.14% w/v fluoride ion)

Purpose

Anticavity toopaste

Use

helps protect against cavities

Warnings

Keep out of reach of children under 6 years of age.Do not swallow. If you accidentally swallow more than used for brushing, seek professional assistance or contact a poison control center right away. If an allergic reaction develops, discontinue use immediately.

Directions

- adults and children 2 years of age and and older: Brush teeth thoroughly, preferably after each meal or at least twice a day, or as directed by a dentist.
- do not swallow.
- to minimize swallowing use a pea-sized amount in children under 6.
- supervise children's brushing until good habits are established.
- children under 2 years: ask a dentist.

Inactive Ingredients

WATER, SORBITOL, HYDRATED SILICA, SODIUM LAURYL SULFATE, GLYCERIN, CELLULOSE GUM, FLAVOR, TETRASODIUM PYROPHOSPHATE, ZINC STEARATE, XANTHAN GUM, TITANIUM DIOXIDE, SORBITAN OLEATE, SODIUM SACCHARIN, HYDROXYAPATITE, NIACINAMIDE, TOCOPHERYL ACETATE, XYLITOL

Questions?

1-866-993-4709

Principal Display Panel - 120 g Tube Carton

POP
Playful. Original. Personal
REPAIRS ENAMEL
PREVENTS CAVITIES
FRESHENS BREATH

HINT OF MINT
Fluoride Toothpaste
with Hydroxyapatite &
Vitamins E and B3

NET WT. 4.2 OZ. (120 G)

DIST. LG H&H CO., LTD.
58, SAEMUNAN-RO, JONGNO-GU, SEOUL, KOREA
www.oralcarebypop.com
MADE IN KOREA